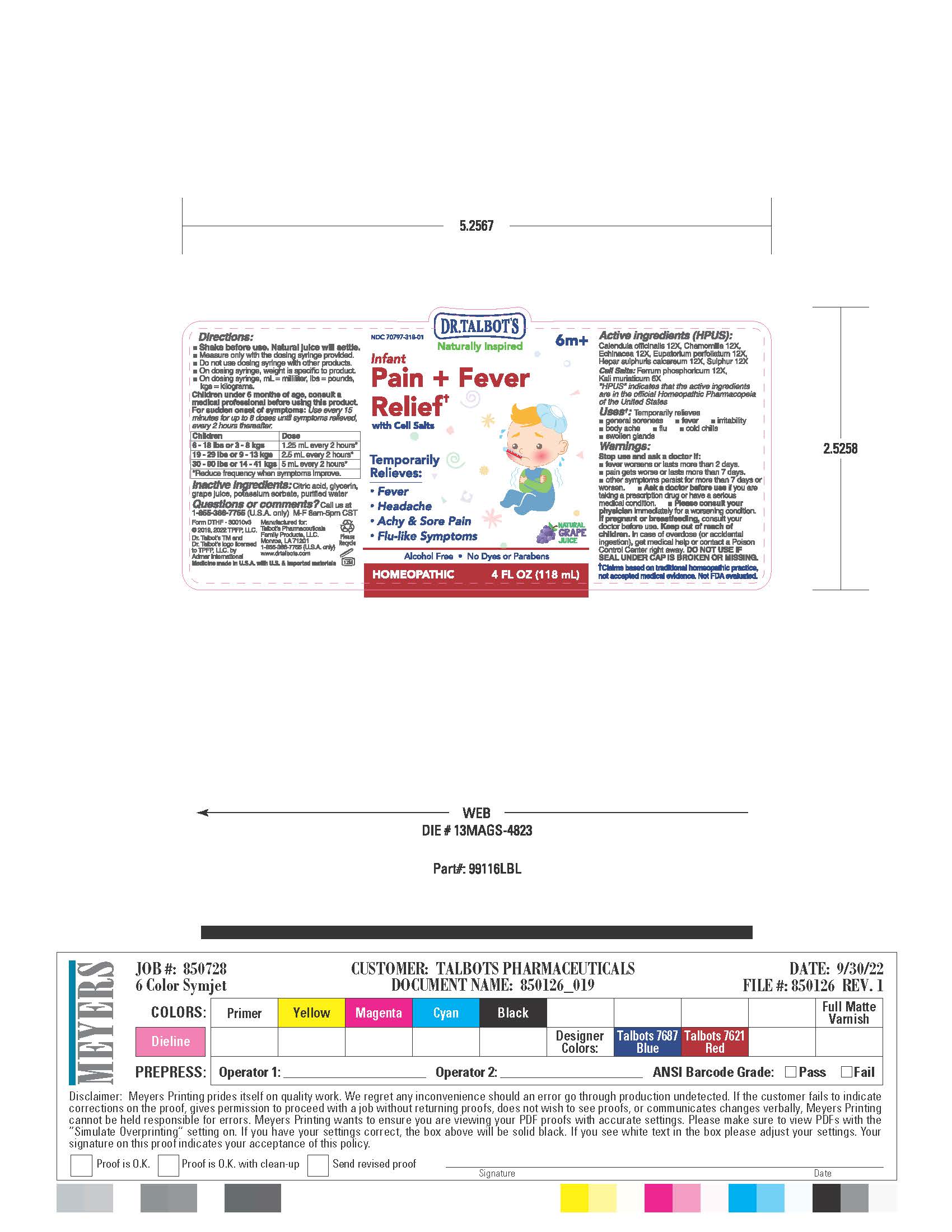 DRUG LABEL: Dr Talbots Infant Pain Fever Relief
NDC: 70797-318 | Form: LIQUID
Manufacturer: Talbot's Pharmaceuticals Family Products,LLC.
Category: homeopathic | Type: HUMAN OTC DRUG LABEL
Date: 20221216

ACTIVE INGREDIENTS: FERROSOFERRIC PHOSPHATE 12 [hp_X]/118 mL; EUPATORIUM PERFOLIATUM FLOWERING TOP 12 [hp_X]/118 mL; POTASSIUM CHLORIDE 6 [hp_X]/118 mL; CALCIUM SULFIDE 12 [hp_X]/118 mL; ECHINACEA ANGUSTIFOLIA 12 [hp_X]/118 mL; MATRICARIA CHAMOMILLA 12 [hp_X]/118 mL; COSMOS SULPHUREUS FLOWERING TOP 12 [hp_X]/118 mL; CALENDULA OFFICINALIS FLOWERING TOP 12 [hp_X]/118 mL
INACTIVE INGREDIENTS: WATER; CITRIC ACID MONOHYDRATE; CONCORD GRAPE JUICE; GLYCERIN; POTASSIUM SORBATE

Acitve Ingredients

Active Ingredients
Calendula officinalis 12X HPUS
Chamomilla 12X HPUS
Echinacea angustifolia 12X HPUS
Eupatorium perfoliatum 12X HPUS
Hepar sulphuris calcareum 12X HPUS
Sulphur 12X HPUS
Cell Salts
Ferrum phosphoricum 12X HPUS
Kali muriaticum 6X HPUS

WARNINGS

Stop use and ask doctor if:

- fever wosens or lasts more than 2 days
- pain gets worse or lasts more than 7 days
- other symptoms persist for more than 7 days or worsen

Pregnant or breastfeeding

If pregnant or breastfeeding, consult your doctor before use.

Keep out of reach of children

Keep out of reach of children. In case of overdoes (or accidental ingestion), get medical help or contact a Poison Control Center right away. DO NOT USE IF SEAL UNDER CAP IS BROKEN OR MISSING.

DOSAGE

Children under 6 months of age, consult a medical professional before using this product.

For sudden onset of symptoms: Use every 15 minutes for up to 8 doses until symptoms relieved, then every 2 hours thereafter.

Children 6 - 18 lbs or 3 - 8 kgs

1.25 ml every 2 hours, reduce frequency when symptoms improve

Children 19 - 29 lbs or 9 - 13 kgs

2.5 ml every 2 hours, reduce frequency when symptoms improve

Children 30 - 90 lbs or 14 - 41 kgs

5 ml every 2 hours, reduce frequency when symptoms improve

INACTIVE INGREDIENTS

Citric acid, glycerin, grape juice, potassium
sorbate, purified water.

QUESTIONS

Questions or comments?
Call us at 1-855-366-7755 (U.S.A. only)
M-F 8am-5pm CST

Purpose

Temporarily Relieves:

- Fever
- headache
- Achy & Sore Pain
- Flu-like Symptoms

DOSAGE

Children under 6 months of age, consult a medical professional before using this product.
For sudden onset of symptoms: Use every 15 minutes for up to 8 doses until symptoms relieved, every 2 hours thereafter.

Usage

Uses: Temproraily relieves

- general sorness
- fever
- irritability
- body ache
- flu
- cold chills
- swollen glands

PRINCIPAL DISPLAY PANEL

LABEL DISPLAY: